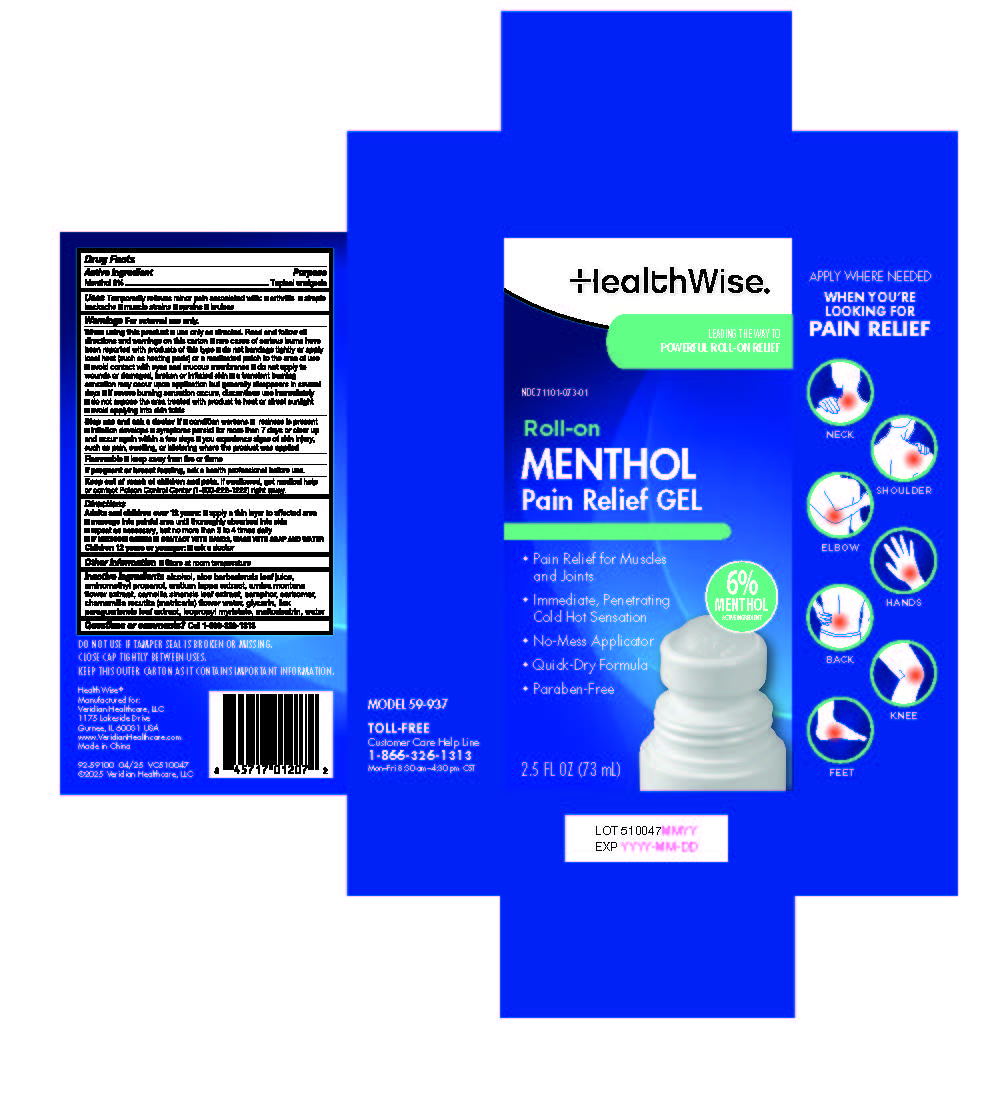 DRUG LABEL: HealthWise Roll-on Menthol Pain Relief Gel
NDC: 71101-073 | Form: GEL
Manufacturer: Veridian Healthcare
Category: otc | Type: HUMAN OTC DRUG LABEL
Date: 20250428

ACTIVE INGREDIENTS: MENTHOL 0.6 g/1 mL
INACTIVE INGREDIENTS: MALTODEXTRIN; ARCTIUM LAPPA WHOLE; ILEX PARAGUARIENSIS LEAF; CAMPHOR (NATURAL); GLYCERIN; ISOPROPYL MYRISTATE; CARBOMER 940; ALCOHOL; AMINOMETHYLPROPANOL; WATER; ALOE VERA LEAF; ARNICA MONTANA FLOWER; CHAMOMILE FLOWER OIL; CAMELLIA SINENSIS LEAF

HealthWise Roll-on Menthol Pain Relief Gel

HealthWise Roll-on Menthol Pain Relief Gel

Active ingredient

Menthol 6%

Purpose

Topical analgesic

Uses

temporarily relieves minor pain associated with:

- arthritis
- simple backache
- muscle strains
- sprains
- bruises

Warnings

For external use only

When using this product

- use only as directed. Read and follow all directions and warnings on this carton.
- avoid contact with eyes and mucous membranes
- rare cases of serious burns have been reported with products of this type
- do not apply to wounds or damaged, broken or irritated skin
- do not bandage tightly or apply local heat (such as heating pads) or a medicated patch to the area of use
- a transient burning sensation may occur upon application but generally disappears in several days
- if severe burning sensation occurs, discontinue use immediately
- do not expose the area treated with product to heat or direct sunlight
- avoid applying into skin folds

Stop use and ask a doctor if

- condition worsens
- redness is present
- irritation develops
- symptoms persist for more than 7 days or clear up and occur again within a few days
- you experience signs of skin injury, such as pain, swelling, or blistering where the product was applied

Flammable■ Keep away from fire or flame

If pregnant or breast-feeding,

ask a health professional before use.

Keep out of reach of children.

If swallowed, get medical help or contact a Poison Control Center (1-800-222-1222) right away.

Directions

adults and children over 12 years:

- apply a thin layer to affected area
- massage into painful area until thoroughly absorbed into skin
- repeat as necessary, but no more than 3 to 4 times daily
- IF MEDICINE COMES IN CONTACT WITH HANDS, WASH WITH SOAP AND WATER

children 12 years or younger:ask a doctor

Inactive ingredients

alcohol, aloe barbadensis leaf juice, aminomethyl propanol, arctium lappa extract, arnica montana flower extract, camellia sinensis leaf extract, camphor, carbomer, chamomilla recutita (matricaria) flower water, glycerin, ilex paraguariensis leaf extract, isopropyl myristate, maltodextrin, water